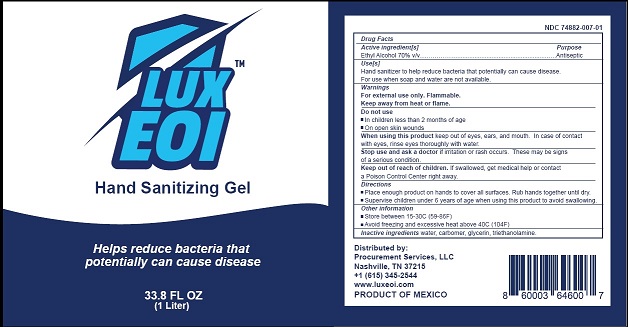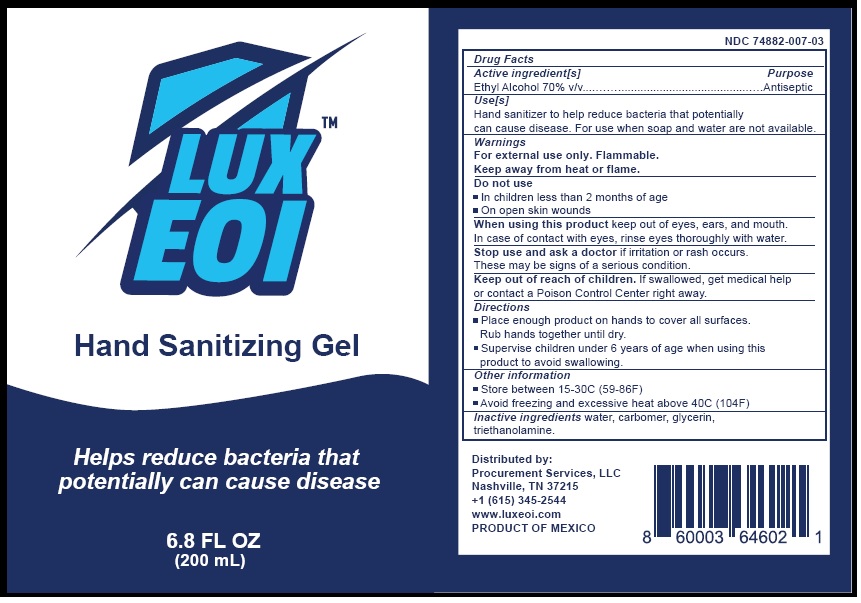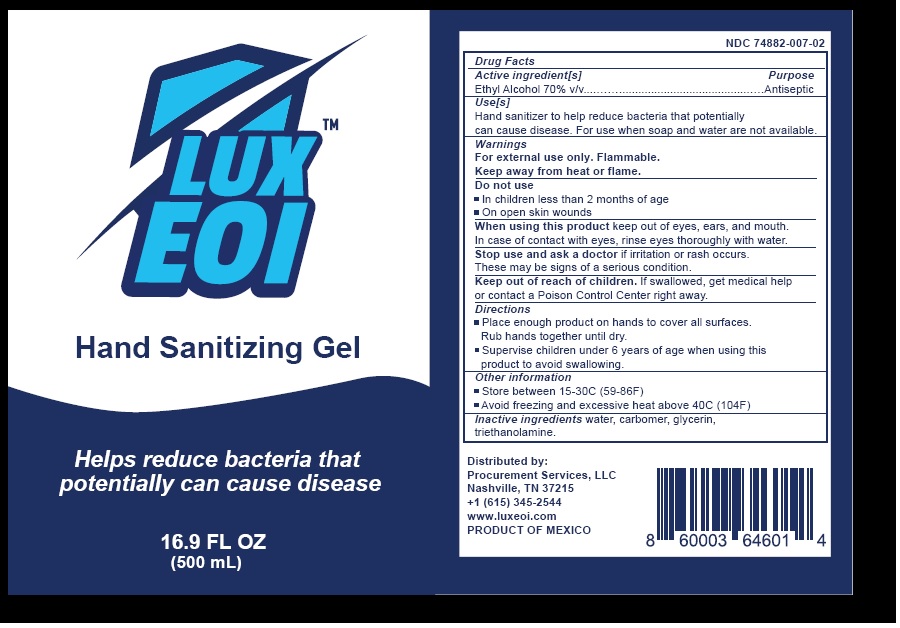 DRUG LABEL: Lux Eoi Hand Sanitizing Gel
NDC: 74882-007 | Form: GEL
Manufacturer: Procurement Services LLC
Category: otc | Type: HUMAN OTC DRUG LABEL
Date: 20200609

ACTIVE INGREDIENTS: ALCOHOL 70 mL/100 mL
INACTIVE INGREDIENTS: WATER; CARBOMER HOMOPOLYMER, UNSPECIFIED TYPE; GLYCERIN; TROLAMINE

Lux Eoi Hand Sanitizing Gel

Drug Facts

Active ingredients

Ethyl Alcohol 70%

Purpose

Antiseptic

INDICATIONS AND USAGE

Use[s]
Hand sanitizer to help reduce bacteria that potentially
can cause disease. For use when soap and water are not available.

Warnings
For external use only. Flammable.
Keep away from heat or flame.

Do not use
• In children less than 2 months of age
• On open skin wounds

When using this product keep out of eyes, ears, and mouth.
In case of contact with eyes, rinse eyes thoroughly with water.

Stop use and ask a doctor if irritation or rash occurs.
These may be signs of a serious condition.

Keep out of reach of children. If swallowed, get medical help
or contact a Poison Control Center right away.

Directions
• Place enough product on hands to cover all surfaces.
Rub hands together until dry.
• Supervise children under 6 years of age when using this
product to avoid swallowing.

Other information
• Store between 15-30C (59-86F)
• Avoid freezing and excessive heat above 40C (104F)

Inactive ingredientswater, carbomer, glycerin,
triethanolamine.

Package Labeling

LUX™

EOI

Hand Sanitizing Gel

Helps reduce bacteria that

potentially can cause disease

33.8 FL OZ

(1 Liter)

NDC 74882-007-01

Distributed by
Procurement Services LLC
Nashville, TN 37215
+1 (615) 345-2544
www.luxeoi.com
PRODUCT OF MEXICO

1 Liter Bottle

500 mL Bottle

200mL Bottle

res